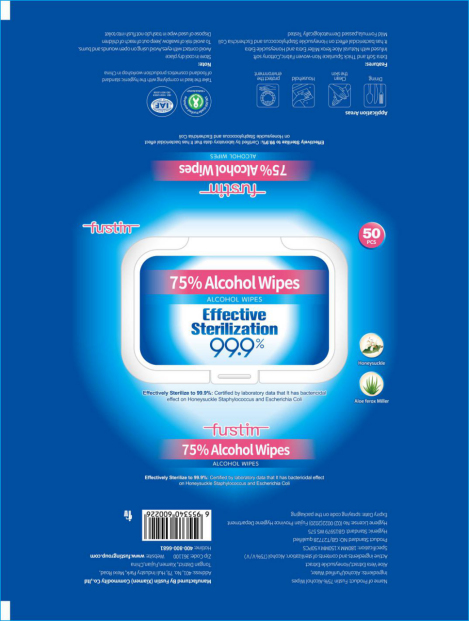 DRUG LABEL: FUSTIN 75% ALCOHOL WIPES
NDC: 42129-007 | Form: CLOTH
Manufacturer: Fustin (Xiamen) Commodity Co., Ltd.
Category: otc | Type: HUMAN OTC DRUG LABEL
Date: 20200427

ACTIVE INGREDIENTS: ALCOHOL 165 mL/50 1
INACTIVE INGREDIENTS: ALOE VERA LEAF; WATER

DOSAGE AND ADMINISTRATION

Keep away from flame or high heat.

INACTIVE INGREDIENT

Purified Water

Aloe Vera Extract

Honeysuckle Extract

INDICATIONS AND USAGE

Open the upper cover, open the unsealing glue, pull out the wet wipes.

ACTIVE INGREDIENT

Alcohol

keep out of children

PURPOSE

Disinfection
Sterilization
No Rinseing

WARNINGS

Please place it out of reach of infants to avoid eating by mistake.his product is insoluble in water, please throw it into the garbage can after use.